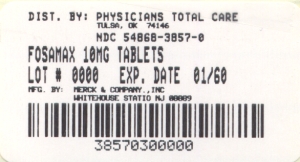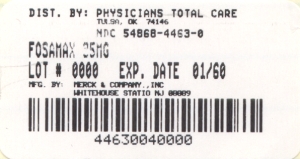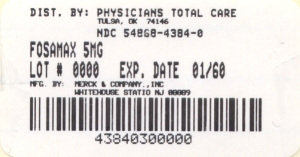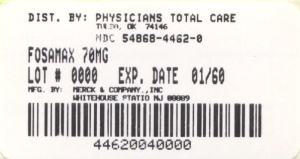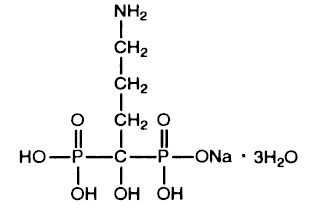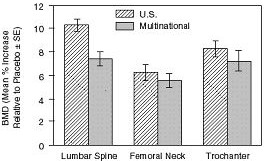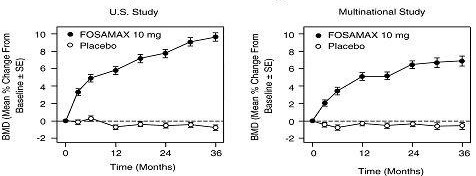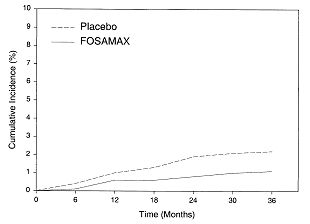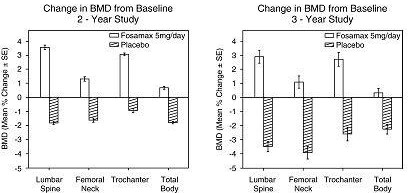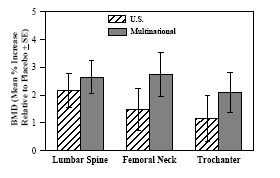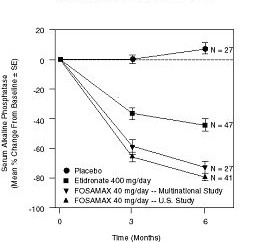 DRUG LABEL: Fosamax
NDC: 54868-4384 | Form: TABLET
Manufacturer: Physicians Total Care, Inc.
Category: prescription | Type: HUMAN PRESCRIPTION DRUG LABEL
Date: 20100305

ACTIVE INGREDIENTS: ALENDRONATE SODIUM 5 mg/1 1
INACTIVE INGREDIENTS: CELLULOSE, MICROCRYSTALLINE; ANHYDROUS LACTOSE; CROSCARMELLOSE SODIUM; MAGNESIUM STEARATE

DESCRIPTION

FOSAMAX1 (alendronate sodium) is a bisphosphonate that acts as a specific inhibitor of osteoclast-mediated bone resorption. Bisphosphonates are synthetic analogs of pyrophosphate that bind to the hydroxyapatite found in bone.

Alendronate sodium is chemically described as (4-amino-1-hydroxybutylidene) bisphosphonic acid monosodium salt trihydrate.

The empirical formula of alendronate sodium is C4H12NNaO7P2•3H2O and its formula weight is 325.12. The structural formula is:

Alendronate sodium is a white, crystalline, nonhygroscopic powder. It is soluble in water, very slightly soluble in alcohol, and practically insoluble in chloroform.

Tablets FOSAMAX for oral administration contain 6.53, 13.05, 45.68, 52.21 or 91.37 mg of alendronate monosodium salt trihydrate, which is the molar equivalent of 5, 10, 35, 40 and 70 mg, respectively, of free acid, and the following inactive ingredients: microcrystalline cellulose, anhydrous lactose, croscarmellose sodium, and magnesium stearate. Tablets FOSAMAX 10 mg also contain carnauba wax.

Each bottle of the oral solution contains 91.35 mg of alendronate monosodium salt trihydrate, which is the molar equivalent to 70 mg of free acid. Each bottle also contains the following inactive ingredients: sodium citrate dihydrate and citric acid anhydrous as buffering agents, sodium saccharin, artificial raspberry flavor, and purified water. Added as preservatives are sodium propylparaben 0.0225% and sodium butylparaben 0.0075%.

1

Registered trademark of MERCK & CO., Inc.
COPYRIGHT © 1995, 1997, 2000 MERCK & CO., Inc.
All rights reserved

CLINICAL PHARMACOLOGY

Mechanism of Action

Animal studies have indicated the following mode of action. At the cellular level, alendronate shows preferential localization to sites of bone resorption, specifically under osteoclasts. The osteoclasts adhere normally to the bone surface but lack the ruffled border that is indicative of active resorption. Alendronate does not interfere with osteoclast recruitment or attachment, but it does inhibit osteoclast activity. Studies in mice on the localization of radioactive [^3H]alendronate in bone showed about 10-fold higher uptake on osteoclast surfaces than on osteoblast surfaces. Bones examined 6 and 49 days after [^3H]alendronate administration in rats and mice, respectively, showed that normal bone was formed on top of the alendronate, which was incorporated inside the matrix. While incorporated in bone matrix, alendronate is not pharmacologically active. Thus, alendronate must be continuously administered to suppress osteoclasts on newly formed resorption surfaces. Histomorphometry in baboons and rats showed that alendronate treatment reduces bone turnover (i.e., the number of sites at which bone is remodeled). In addition, bone formation exceeds bone resorption at these remodeling sites, leading to progressive gains in bone mass.

Pharmacokinetics Absorption

Relative to an intravenous (IV) reference dose, the mean oral bioavailability of alendronate in women was 0.64% for doses ranging from 5 to 70 mg when administered after an overnight fast and two hours before a standardized breakfast. Oral bioavailability of the 10 mg tablet in men (0.59%) was similar to that in women when administered after an overnight fast and 2 hours before breakfast.

FOSAMAX 70 mg oral solution and FOSAMAX 70 mg tablet are equally bioavailable.

A study examining the effect of timing of a meal on the bioavailability of alendronate was performed in 49 postmenopausal women. Bioavailability was decreased (by approximately 40%) when 10 mg alendronate was administered either 0.5 or 1 hour before a standardized breakfast, when compared to dosing 2 hours before eating. In studies of treatment and prevention of osteoporosis, alendronate was effective when administered at least 30 minutes before breakfast.

Bioavailability was negligible whether alendronate was administered with or up to two hours after a standardized breakfast. Concomitant administration of alendronate with coffee or orange juice reduced bioavailability by approximately 60%.

Distribution

Preclinical studies (in male rats) show that alendronate transiently distributes to soft tissues following 1 mg/kg IV administration but is then rapidly redistributed to bone or excreted in the urine. The mean steady-state volume of distribution, exclusive of bone, is at least 28 L in humans. Concentrations of drug in plasma following therapeutic oral doses are too low (less than 5 ng/mL) for analytical detection. Protein binding in human plasma is approximately 78%.

Metabolism

There is no evidence that alendronate is metabolized in animals or humans.

Excretion

Following a single IV dose of [^14C]alendronate, approximately 50% of the radioactivity was excreted in the urine within 72 hours and little or no radioactivity was recovered in the feces. Following a single 10 mg IV dose, the renal clearance of alendronate was 71 mL/min (64, 78; 90% confidence interval [CI]), and systemic clearance did not exceed 200 mL/min. Plasma concentrations fell by more than 95% within 6 hours following IV administration. The terminal half-life in humans is estimated to exceed 10 years, probably reflecting release of alendronate from the skeleton. Based on the above, it is estimated that after 10 years of oral treatment with FOSAMAX (10 mg daily) the amount of alendronate released daily from the skeleton is approximately 25% of that absorbed from the gastrointestinal tract.

Special Populations Pediatric:

The oral bioavailability in children was similar to that observed in adults; however, FOSAMAX is not indicated for use in children (see PRECAUTIONS, Pediatric Use).

Gender:

Bioavailability and the fraction of an IV dose excreted in urine were similar in men and women.

Geriatric:

Bioavailability and disposition (urinary excretion) were similar in elderly and younger patients. No dosage adjustment is necessary (see DOSAGE AND ADMINISTRATION).

Race:

Pharmacokinetic differences due to race have not been studied.

Renal Insufficiency:

Preclinical studies show that, in rats with kidney failure, increasing amounts of drug are present in plasma, kidney, spleen, and tibia. In healthy controls, drug that is not deposited in bone is rapidly excreted in the urine. No evidence of saturation of bone uptake was found after 3 weeks dosing with cumulative IV doses of 35 mg/kg in young male rats. Although no clinical information is available, it is likely that, as in animals, elimination of alendronate via the kidney will be reduced in patients with impaired renal function. Therefore, somewhat greater accumulation of alendronate in bone might be expected in patients with impaired renal function.

No dosage adjustment is necessary for patients with mild-to-moderate renal insufficiency (creatinine clearance 35 to 60 mL/min). FOSAMAX is not recommended for patients with more severe renal insufficiency (creatinine clearance less than 35 mL/min) due to lack of experience with alendronate in renal failure.

Hepatic Insufficiency:

As there is evidence that alendronate is not metabolized or excreted in the bile, no studies were conducted in patients with hepatic insufficiency. No dosage adjustment is necessary.

Drug Interactions

(also see PRECAUTIONS, Drug Interactions)

Intravenous ranitidine was shown to double the bioavailability of oral alendronate. The clinical significance of this increased bioavailability and whether similar increases will occur in patients given oral H2-antagonists is unknown.

In healthy subjects, oral prednisone (20 mg three times daily for five days) did not produce a clinically meaningful change in the oral bioavailability of alendronate (a mean increase ranging from 20 to 44%).

Products containing calcium and other multivalent cations are likely to interfere with absorption of alendronate.

Pharmacodynamics

Alendronate is a bisphosphonate that binds to bone hydroxyapatite and specifically inhibits the activity of osteoclasts, the bone-resorbing cells. Alendronate reduces bone resorption with no direct effect on bone formation, although the latter process is ultimately reduced because bone resorption and formation are coupled during bone turnover.

Osteoporosis in postmenopausal women

Osteoporosis is characterized by low bone mass that leads to an increased risk of fracture. The diagnosis can be confirmed by the finding of low bone mass, evidence of fracture on x-ray, a history of osteoporotic fracture, or height loss or kyphosis, indicative of vertebral (spinal) fracture. Osteoporosis occurs in both males and females but is most common among women following the menopause, when bone turnover increases and the rate of bone resorption exceeds that of bone formation. These changes result in progressive bone loss and lead to osteoporosis in a significant proportion of women over age 50. Fractures, usually of the spine, hip, and wrist, are the common consequences. From age 50 to age 90, the risk of hip fracture in white women increases 50-fold and the risk of vertebral fracture 15- to 30-fold. It is estimated that approximately 40% of 50-year-old women will sustain one or more osteoporosis-related fractures of the spine, hip, or wrist during their remaining lifetimes. Hip fractures, in particular, are associated with substantial morbidity, disability, and mortality.

Daily oral doses of alendronate (5, 20, and 40 mg for six weeks) in postmenopausal women produced biochemical changes indicative of dose-dependent inhibition of bone resorption, including decreases in urinary calcium and urinary markers of bone collagen degradation (such as deoxypyridinoline and cross-linked N-telopeptides of type I collagen). These biochemical changes tended to return toward baseline values as early as 3 weeks following the discontinuation of therapy with alendronate and did not differ from placebo after 7 months.

Long-term treatment of osteoporosis with FOSAMAX 10 mg/day (for up to five years) reduced urinary excretion of markers of bone resorption, deoxypyridinoline and cross-linked N-telopeptides of type l collagen, by approximately 50% and 70%, respectively, to reach levels similar to those seen in healthy premenopausal women. Similar decreases were seen in patients in osteoporosis prevention studies who received FOSAMAX 5 mg/day. The decrease in the rate of bone resorption indicated by these markers was evident as early as one month and at three to six months reached a plateau that was maintained for the entire duration of treatment with FOSAMAX. In osteoporosis treatment studies FOSAMAX 10 mg/day decreased the markers of bone formation, osteocalcin and bone specific alkaline phosphatase by approximately 50%, and total serum alkaline phosphatase by approximately 25 to 30% to reach a plateau after 6 to 12 months. In osteoporosis prevention studies FOSAMAX 5 mg/day decreased osteocalcin and total serum alkaline phosphatase by approximately 40% and 15%, respectively. Similar reductions in the rate of bone turnover were observed in postmenopausal women during one-year studies with once weekly FOSAMAX 70 mg for the treatment of osteoporosis and once weekly FOSAMAX 35 mg for the prevention of osteoporosis. These data indicate that the rate of bone turnover reached a new steady-state, despite the progressive increase in the total amount of alendronate deposited within bone.

As a result of inhibition of bone resorption, asymptomatic reductions in serum calcium and phosphate concentrations were also observed following treatment with FOSAMAX. In the long-term studies, reductions from baseline in serum calcium (approximately 2%) and phosphate (approximately 4 to 6%) were evident the first month after the initiation of FOSAMAX 10 mg. No further decreases in serum calcium were observed for the five-year duration of treatment; however, serum phosphate returned toward prestudy levels during years three through five. Similar reductions were observed with FOSAMAX 5 mg/day. In one-year studies with once weekly FOSAMAX 35 and 70 mg, similar reductions were observed at 6 and 12 months. The reduction in serum phosphate may reflect not only the positive bone mineral balance due to FOSAMAX but also a decrease in renal phosphate reabsorption.

Osteoporosis in men

Treatment of men with osteoporosis with FOSAMAX 10 mg/day for two years reduced urinary excretion of cross-linked N-telopeptides of type I collagen by approximately 60% and bone-specific alkaline phosphatase by approximately 40%. Similar reductions were observed in a one-year study in men with osteoporosis receiving once weekly FOSAMAX 70 mg.

Glucocorticoid-induced Osteoporosis

Sustained use of glucocorticoids is commonly associated with development of osteoporosis and resulting fractures (especially vertebral, hip, and rib). It occurs both in males and females of all ages. Osteoporosis occurs as a result of inhibited bone formation and increased bone resorption resulting in net bone loss. Alendronate decreases bone resorption without directly inhibiting bone formation.

In clinical studies of up to two years' duration, FOSAMAX 5 and 10 mg/day reduced cross-linked N-telopeptides of type I collagen (a marker of bone resorption) by approximately 60% and reduced bone-specific alkaline phosphatase and total serum alkaline phosphatase (markers of bone formation) by approximately 15 to 30% and 8 to 18%, respectively. As a result of inhibition of bone resorption, FOSAMAX 5 and 10 mg/day induced asymptomatic decreases in serum calcium (approximately 1 to 2%) and serum phosphate (approximately 1 to 8%).

Paget's disease of bone

Paget's disease of bone is a chronic, focal skeletal disorder characterized by greatly increased and disorderly bone remodeling. Excessive osteoclastic bone resorption is followed by osteoblastic new bone formation, leading to the replacement of the normal bone architecture by disorganized, enlarged, and weakened bone structure.

Clinical manifestations of Paget's disease range from no symptoms to severe morbidity due to bone pain, bone deformity, pathological fractures, and neurological and other complications. Serum alkaline phosphatase, the most frequently used biochemical index of disease activity, provides an objective measure of disease severity and response to therapy.

FOSAMAX decreases the rate of bone resorption directly, which leads to an indirect decrease in bone formation. In clinical trials, FOSAMAX 40 mg once daily for six months produced significant decreases in serum alkaline phosphatase as well as in urinary markers of bone collagen degradation. As a result of the inhibition of bone resorption, FOSAMAX induced generally mild, transient, and asymptomatic decreases in serum calcium and phosphate.

Clinical Studies Treatment of Osteoporosis Postmenopausal women Effect on bone mineral density

The efficacy of FOSAMAX 10 mg once daily in postmenopausal women, 44 to 84 years of age, with osteoporosis (lumbar spine bone mineral density [BMD] of at least 2 standard deviations below the premenopausal mean) was demonstrated in four double-blind, placebo-controlled clinical studies of two or three years' duration. These included two three-year, multicenter studies of virtually identical design, one performed in the United States (U.S.) and the other in 15 different countries (Multinational), which enrolled 478 and 516 patients, respectively. The following graph shows the mean increases in BMD of the lumbar spine, femoral neck, and trochanter in patients receiving FOSAMAX 10 mg/day relative to placebo-treated patients at three years for each of these studies.

Osteoporosis Treatment Studies in Postmenopausal Women: Increase in BMD: FOSAMAX 10mg/day at Three Years

At three years significant increases in BMD, relative both to baseline and placebo, were seen at each measurement site in each study in patients who received FOSAMAX 10 mg/day. Total body BMD also increased significantly in each study, suggesting that the increases in bone mass of the spine and hip did not occur at the expense of other skeletal sites. Increases in BMD were evident as early as three months and continued throughout the three years of treatment. (See figures below for lumbar spine results.) In the two-year extension of these studies, treatment of 147 patients with FOSAMAX 10 mg/day resulted in continued increases in BMD at the lumbar spine and trochanter (absolute additional increases between years 3 and 5: lumbar spine, 0.94%; trochanter, 0.88%). BMD at the femoral neck, forearm and total body were maintained. FOSAMAX was similarly effective regardless of age, race, baseline rate of bone turnover, and baseline BMD in the range studied (at least 2 standard deviations below the premenopausal mean). Thus, overall FOSAMAX reverses the loss of bone mineral density, a central factor in the progression of osteoporosis.

Osteoporosis Treatment Studies in Postmenopausal Women: Time Course of Effect of FOSAMAX 10 mg/day Versus Placebo: Lumbar Spine BMD Percent Change From Baseline

In patients with postmenopausal osteoporosis treated with FOSAMAX 10 mg/day for one or two years, the effects of treatment withdrawal were assessed. Following discontinuation, there were no further increases in bone mass and the rates of bone loss were similar to those of the placebo groups. These data indicate that continued treatment with FOSAMAX is required to maintain the effect of the drug.

The therapeutic equivalence of once weekly FOSAMAX 70 mg (n=519) and FOSAMAX 10 mg daily (n=370) was demonstrated in a one-year, double-blind, multicenter study of postmenopausal women with osteoporosis. In the primary analysis of completers, the mean increases from baseline in lumbar spine BMD at one year were 5.1% (4.8, 5.4%; 95% CI) in the 70-mg once-weekly group (n=440) and 5.4% (5.0, 5.8%; 95% CI) in the 10-mg daily group (n=330). The two treatment groups were also similar with regard to BMD increases at other skeletal sites. The results of the intention-to-treat analysis were consistent with the primary analysis of completers.

Effect on fracture incidence

Data on the effects of FOSAMAX on fracture incidence are derived from three clinical studies: 1) U.S. and Multinational combined: a study of patients with a BMD T-score at or below minus 2.5 with or without a prior vertebral fracture, 2) Three-Year Study of the Fracture Intervention Trial (FIT): a study of patients with at least one baseline vertebral fracture, and 3) Four-Year Study of FIT: a study of patients with low bone mass but without a baseline vertebral fracture.

To assess the effects of FOSAMAX on the incidence of vertebral fractures (detected by digitized radiography; approximately one third of these were clinically symptomatic), the U.S. and Multinational studies were combined in an analysis that compared placebo to the pooled dosage groups of FOSAMAX (5 or 10 mg for three years or 20 mg for two years followed by 5 mg for one year). There was a statistically significant reduction in the proportion of patients treated with FOSAMAX experiencing one or more new vertebral fractures relative to those treated with placebo (3.2% vs. 6.2%; a 48% relative risk reduction). A reduction in the total number of new vertebral fractures (4.2 vs. 11.3 per 100 patients) was also observed. In the pooled analysis, patients who received FOSAMAX had a loss in stature that was statistically significantly less than was observed in those who received placebo (-3.0 mm vs. -4.6 mm).

The Fracture Intervention Trial (FIT) consisted of two studies in postmenopausal women: the Three-Year Study of patients who had at least one baseline radiographic vertebral fracture and the Four-Year Study of patients with low bone mass but without a baseline vertebral fracture. In both studies of FIT, 96% of randomized patients completed the studies (i.e., had a closeout visit at the scheduled end of the study); approximately 80% of patients were still taking study medication upon completion.

Fracture Intervention Trial: Three-Year Study (patients with at least one baseline radiographic vertebral fracture)

This randomized, double-blind, placebo-controlled, 2027-patient study (FOSAMAX, n=1022; placebo, n=1005) demonstrated that treatment with FOSAMAX resulted in statistically significant reductions in fracture incidence at three years as shown in the table below.

Effect of FOSAMAX on Fracture Incidence in the Three-Year Study of FIT (patients with vertebral fracture at baseline)
 | FOSAMAX (n=1022) | Percent of Patients Placebo (n=1005) | Absolute Reduction in Fracture Incidence | Relative Reduction in Fracture Risk %
Patients with: Vertebral fractures (diagnosed by X-ray)* ≥ 1 new vertebral fracture | 7.9 | 15.0 | 7.1 | 47†
≥ 2 new vertebral fractures | 0.5 | 4.9 | 4.4 | 90†
Clinical (symptomatic) fractures Any clinical (symptomatic) fracture | 13.8 | 18.1 | 4.3 | 26‡
≥ 1 clinical (symptomatic) vertebral fracture | 2.3 | 5.0 | 2.7 | 54§
Hip fracture | 1.1 | 2.2 | 1.1 | 51¶
Wrist (forearm) fracture | 2.2 | 4.1 | 1.9 | 48¶

* Number evaluable for vertebral fractures: FOSAMAX, n=984; placebo, n=966
† p less than 0.001
‡ p=0.007
§ p less than 0.01
¶
p less than 0.05

Furthermore, in this population of patients with baseline vertebral fracture, treatment with FOSAMAX significantly reduced the incidence of hospitalizations (25.0% vs. 30.7%).

In the Three-Year Study of FIT, fractures of the hip occurred in 22 (2.2%) of 1005 patients on placebo and 11 (1.1%) of 1022 patients on FOSAMAX, p=0.047. The figure below displays the cumulative incidence of hip fractures in this study.

Cumulative Incidence of Hip Fractures in the Three-Year Study of FIT (patients with radiographic vertebral fracture at baseline)

Fracture Intervention Trial: Four-Year Study (patients with low bone mass but without a baseline radiographic vertebral fracture)

This randomized, double-blind, placebo-controlled, 4432-patient study (FOSAMAX, n=2214; placebo, n=2218) further investigated the reduction in fracture incidence due to FOSAMAX. The intent of the study was to recruit women with osteoporosis, defined as a baseline femoral neck BMD at least two standard deviations below the mean for young adult women. However, due to subsequent revisions to the normative values for femoral neck BMD, 31% of patients were found not to meet this entry criterion and thus this study included both osteoporotic and non-osteoporotic women. The results are shown in the table below for the patients with osteoporosis.

Effect of FOSAMAX on Fracture Incidence in Osteoporotic* Patients in the Four-Year Study of FIT (patients without vertebral fracture at baseline)
 | FOSAMAX (n=1545) | Percent of Patients Placebo (n=1521) | Absolute Reduction in Fracture Incidence | Relative Reduction in Fracture Risk (%)
Patients with:
Vertebral fractures (diagnosed by X-ray)†
≥ 1 new vertebral fracture | 2.5 | 4.8 | 2.3 | 48‡
≥ 2 new vertebral fractures | 0.1 | 0.6 | 0.5 | 78§
Clinical (symptomatic) fractures
Any clinical (symptomatic) fracture | 12.9 | 16.2 | 3.3 | 22¶
≥ 1 clinical (symptomatic) vertebral fracture | 1.0 | 1.6 | 0.6 | 41(NS)#
Hip fracture | 1.0 | 1.4 | 0.4 | 29(NS)#
Wrist (forearm) fracture | 3.9 | 3.8 | -0.1 | NS#

* Baseline femoral neck BMD at least 2 SD below the mean for young adult women
† Number evaluable for vertebral fractures: FOSAMAX, n=1426; placebo, n=1428
‡ p less than 0.001
§ p=0.035
¶ p=0.01
#
Not significant. This study was not powered to detect differences at these sites.
Fracture results across studies

In the Three-Year Study of FIT, FOSAMAX reduced the percentage of women experiencing at least one new radiographic vertebral fracture from 15.0% to 7.9% (47% relative risk reduction, p less than 0.001); in the Four-Year Study of FIT, the percentage was reduced from 3.8% to 2.1% (44% relative risk reduction, p=0.001); and in the combined U.S./Multinational studies, from 6.2% to 3.2% (48% relative risk reduction, p=0.034).

FOSAMAX reduced the percentage of women experiencing multiple (two or more) new vertebral fractures from 4.2% to 0.6% (87% relative risk reduction, p less than 0.001) in the combined U.S./Multinational studies and from 4.9% to 0.5% (90% relative risk reduction, p less than 0.001) in the Three-Year Study of FIT. In the Four-Year Study of FIT, FOSAMAX reduced the percentage of osteoporotic women experiencing multiple vertebral fractures from 0.6% to 0.1% (78% relative risk reduction, p=0.035).

Thus, FOSAMAX reduced the incidence of radiographic vertebral fractures in osteoporotic women whether or not they had a previous radiographic vertebral fracture.

FOSAMAX, over a three- or four-year period, was associated with statistically significant reductions in loss of height vs. placebo in patients with and without baseline radiographic vertebral fractures. At the end of the FIT studies the between-treatment group differences were 3.2 mm in the Three-Year Study and 1.3 mm in the Four-Year Study.

Bone histology

Bone histology in 270 postmenopausal patients with osteoporosis treated with FOSAMAX at doses ranging from 1 to 20 mg/day for one, two, or three years revealed normal mineralization and structure, as well as the expected decrease in bone turnover relative to placebo. These data, together with the normal bone histology and increased bone strength observed in rats and baboons exposed to long-term alendronate treatment, support the conclusion that bone formed during therapy with FOSAMAX is of normal quality.

Men

The efficacy of FOSAMAX in men with hypogonadal or idiopathic osteoporosis was demonstrated in two clinical studies.

A two-year, double-blind, placebo-controlled, multicenter study of FOSAMAX 10 mg once daily enrolled a total of 241 men between the ages of 31 and 87 (mean, 63). All patients in the trial had either: 1) a BMD T-score less than or equal to -2 at the femoral neck and ≤-1 at the lumbar spine, or 2) a baseline osteoporotic fracture and a BMD T-score less than or equal to -1 at the femoral neck. At two years, the mean increases relative to placebo in BMD in men receiving FOSAMAX 10 mg/day were significant at the following sites: lumbar spine, 5.3%; femoral neck, 2.6%; trochanter, 3.1%; and total body, 1.6%. Treatment with FOSAMAX also reduced height loss (FOSAMAX, -0.6 mm vs. placebo, -2.4 mm).

A one-year, double-blind, placebo-controlled, multicenter study of once weekly FOSAMAX 70 mg enrolled a total of 167 men between the ages of 38 and 91 (mean, 66). Patients in the study had either: 1) a BMD T-score less than or equal to -2 at the femoral neck and less than or equal to -1 at the lumbar spine, 2) a BMD T-score less than or equal to -2 at the lumbar spine and less than or equal to -1 at the femoral neck, or 3) a baseline osteoporotic fracture and a BMD T-score less than or equal to -1 at the femoral neck. At one year, the mean increases relative to placebo in BMD in men receiving FOSAMAX 70 mg once weekly were significant at the following sites: lumbar spine, 2.8%; femoral neck, 1.9%; trochanter, 2.0%; and total body, 1.2%. These increases in BMD were similar to those seen at one year in the 10 mg once-daily study.

In both studies, BMD responses were similar regardless of age (greater than or equal to 65 years vs. less than 65 years), gonadal function (baseline testosterone less than 9 ng/dL vs. greater than or equal to 9 ng/dL), or baseline BMD (femoral neck and lumbar spine T-score less than or equal to -2.5 vs. greater than -2.5).

Prevention of osteoporosis in postmenopausal women

Prevention of bone loss was demonstrated in two double-blind, placebo-controlled studies of postmenopausal women 40-60 years of age. One thousand six hundred nine patients (FOSAMAX 5 mg/day; n=498) who were at least six months postmenopausal were entered into a two-year study without regard to their baseline BMD. In the other study, 447 patients (FOSAMAX 5 mg/day; n=88), who were between six months and three years postmenopause, were treated for up to three years. In the placebo-treated patients BMD losses of approximately 1% per year were seen at the spine, hip (femoral neck and trochanter) and total body. In contrast, FOSAMAX 5 mg/day prevented bone loss in the majority of patients and induced significant increases in mean bone mass at each of these sites (see figures below). In addition, FOSAMAX 5 mg/day reduced the rate of bone loss at the forearm by approximately half relative to placebo. FOSAMAX 5 mg/day was similarly effective in this population regardless of age, time since menopause, race and baseline rate of bone turnover.

Osteoporosis Prevention Studies in Postmenopausal Women

The therapeutic equivalence of once weekly FOSAMAX 35 mg (n=362) and FOSAMAX 5 mg daily (n=361) was demonstrated in a one-year, double-blind, multicenter study of postmenopausal women without osteoporosis. In the primary analysis of completers, the mean increases from baseline in lumbar spine BMD at one year were 2.9% (2.6, 3.2%; 95% CI) in the 35-mg once-weekly group (n=307) and 3.2% (2.9, 3.5%; 95% CI) in the 5-mg daily group (n=298). The two treatment groups were also similar with regard to BMD increases at other skeletal sites. The results of the intention-to-treat analysis were consistent with the primary analysis of completers.

Bone histology

Bone histology was normal in the 28 patients biopsied at the end of three years who received FOSAMAX at doses of up to 10 mg/day.

Concomitant use with estrogen/hormone replacement therapy (HRT)

The effects on BMD of treatment with FOSAMAX 10 mg once daily and conjugated estrogen (0.625 mg/day) either alone or in combination were assessed in a two-year, double-blind, placebo-controlled study of hysterectomized postmenopausal osteoporotic women (n=425). At two years, the increases in lumbar spine BMD from baseline were significantly greater with the combination (8.3%) than with either estrogen or FOSAMAX alone (both 6.0%).

The effects on BMD when FOSAMAX was added to stable doses (for at least one year) of HRT (estrogen ± progestin) were assessed in a one-year, double-blind, placebo-controlled study in postmenopausal osteoporotic women (n=428). The addition of FOSAMAX 10 mg once daily to HRT produced, at one year, significantly greater increases in lumbar spine BMD (3.7%) vs. HRT alone (1.1%).

In these studies, significant increases or favorable trends in BMD for combined therapy compared with HRT alone were seen at the total hip, femoral neck, and trochanter. No significant effect was seen for total body BMD.

Histomorphometric studies of transiliac biopsies in 92 subjects showed normal bone architecture. Compared to placebo there was a 98% suppression of bone turnover (as assessed by mineralizing surface) after 18 months of combined treatment with FOSAMAX and HRT, 94% on FOSAMAX alone, and 78% on HRT alone. The long-term effects of combined FOSAMAX and HRT on fracture occurrence and fracture healing have not been studied.

Glucocorticoid-induced osteoporosis

The efficacy of FOSAMAX 5 and 10 mg once daily in men and women receiving glucocorticoids (at least 7.5 mg/day of prednisone or equivalent) was demonstrated in two, one-year, double-blind, randomized, placebo-controlled, multicenter studies of virtually identical design, one performed in the United States and the other in 15 different countries (Multinational [which also included FOSAMAX 2.5 mg/day]). These studies enrolled 232 and 328 patients, respectively, between the ages of 17 and 83 with a variety of glucocorticoid-requiring diseases. Patients received supplemental calcium and vitamin D. The following figure shows the mean increases relative to placebo in BMD of the lumbar spine, femoral neck, and trochanter in patients receiving FOSAMAX 5 mg/day for each study.

Studies in Glucocorticoid-Treated Patients: Increase in BMD: FOSAMAX 5 mg/day at One Year

After one year, significant increases relative to placebo in BMD were seen in the combined studies at each of these sites in patients who received FOSAMAX 5 mg/day. In the placebo-treated patients, a significant decrease in BMD occurred at the femoral neck (-1.2%), and smaller decreases were seen at the lumbar spine and trochanter. Total body BMD was maintained with FOSAMAX 5 mg/day. The increases in BMD with FOSAMAX 10 mg/day were similar to those with FOSAMAX 5 mg/day in all patients except for postmenopausal women not receiving estrogen therapy. In these women, the increases (relative to placebo) with FOSAMAX 10 mg/day were greater than those with FOSAMAX 5 mg/day at the lumbar spine (4.1% vs. 1.6%) and trochanter (2.8% vs. 1.7%), but not at other sites. FOSAMAX was effective regardless of dose or duration of glucocorticoid use. In addition, FOSAMAX was similarly effective regardless of age (less than 65 vs. greater than or equal to 65 years), race (Caucasian vs. other races), gender, underlying disease, baseline BMD, baseline bone turnover, and use with a variety of common medications.

Bone histology was normal in the 49 patients biopsied at the end of one year who received FOSAMAX at doses of up to 10 mg/day.

Of the original 560 patients in these studies, 208 patients who remained on at least 7.5 mg/day of prednisone or equivalent continued into a one-year double-blind extension. After two years of treatment, spine BMD increased by 3.7% and 5.0% relative to placebo with FOSAMAX 5 and 10 mg/day, respectively. Significant increases in BMD (relative to placebo) were also observed at the femoral neck, trochanter, and total body.

After one year, 2.3% of patients treated with FOSAMAX 5 or 10 mg/day (pooled) vs. 3.7% of those treated with placebo experienced a new vertebral fracture (not significant). However, in the population studied for two years, treatment with FOSAMAX (pooled dosage groups: 5 or 10 mg for two years or 2.5 mg for one year followed by 10 mg for one year) significantly reduced the incidence of patients with a new vertebral fracture (FOSAMAX 0.7% vs. placebo 6.8%).

Paget's disease of bone

The efficacy of FOSAMAX 40 mg once daily for six months was demonstrated in two double-blind clinical studies of male and female patients with moderate to severe Paget's disease (alkaline phosphatase at least twice the upper limit of normal): a placebo-controlled, multinational study and a U.S. comparative study with etidronate disodium 400 mg/day. The following figure shows the mean percent changes from baseline in serum alkaline phosphatase for up to six months of randomized treatment.

Studies in Paget's Disease of Bone: Effect on Serum Alkaline Phosphatase of FOSAMAX 40 mg/day Versus Placebo or Etidronate 400 mg/day

At six months the suppression in alkaline phosphatase in patients treated with FOSAMAX was significantly greater than that achieved with etidronate and contrasted with the complete lack of response in placebo-treated patients. Response (defined as either normalization of serum alkaline phosphatase or decrease from baseline greater than or equal to 60%) occurred in approximately 85% of patients treated with FOSAMAX in the combined studies vs. 30% in the etidronate group and 0% in the placebo group. FOSAMAX was similarly effective regardless of age, gender, race, prior use of other bisphosphonates, or baseline alkaline phosphatase within the range studied (at least twice the upper limit of normal).

Bone histology was evaluated in 33 patients with Paget's disease treated with FOSAMAX 40 mg/day for 6 months. As in patients treated for osteoporosis (see Clinical Studies, Treatment of osteoporosis in postmenopausal women, Bone histology), FOSAMAX did not impair mineralization, and the expected decrease in the rate of bone turnover was observed. Normal lamellar bone was produced during treatment with FOSAMAX, even where preexisting bone was woven and disorganized. Overall, bone histology data support the conclusion that bone formed during treatment with FOSAMAX is of normal quality.

ANIMAL PHARMACOLOGY

The relative inhibitory activities on bone resorption and mineralization of alendronate and etidronate were compared in the Schenk assay, which is based on histological examination of the epiphyses of growing rats. In this assay, the lowest dose of alendronate that interfered with bone mineralization (leading to osteomalacia) was 6000-fold the antiresorptive dose. The corresponding ratio for etidronate was one to one. These data suggest that alendronate administered in therapeutic doses is highly unlikely to induce osteomalacia.

INDICATIONS AND USAGE

FOSAMAX is indicated for:

- Treatment and prevention of osteoporosis in postmenopausal women
  - For the treatment of osteoporosis, FOSAMAX increases bone mass and reduces the incidence of fractures, including those of the hip and spine (vertebral compression fractures). Osteoporosis may be confirmed by the finding of low bone mass (for example, at least 2 standard deviations below the premenopausal mean) or by the presence or history of osteoporotic fracture. (See CLINICAL PHARMACOLOGY, Pharmacodynamics.)
  - For the prevention of osteoporosis, FOSAMAX may be considered in postmenopausal women who are at risk of developing osteoporosis and for whom the desired clinical outcome is to maintain bone mass and to reduce the risk of future fracture.
    Bone loss is particularly rapid in postmenopausal women younger than age 60. Risk factors often associated with the development of postmenopausal osteoporosis include early menopause; moderately low bone mass (for example, at least 1 standard deviation below the mean for healthy young adult women); thin body build; Caucasian or Asian race; and family history of osteoporosis. The presence of such risk factors may be important when considering the use of FOSAMAX for prevention of osteoporosis.
- Treatment to increase bone mass in men with osteoporosis
- Treatment of glucocorticoid-induced osteoporosis in men and women receiving glucocorticoids in a daily dosage equivalent to 7.5 mg or greater of prednisone and who have low bone mineral density (see PRECAUTIONS, Glucocorticoid-induced osteoporosis). Patients treated with glucocorticoids should receive adequate amounts of calcium and vitamin D.
- Treatment of Paget's disease of bone in men and women
  - Treatment is indicated in patients with Paget's disease of bone having alkaline phosphatase at least two times the upper limit of normal, or those who are symptomatic, or those at risk for future complications from their disease.

CONTRAINDICATIONS

- Abnormalities of the esophagus which delay esophageal emptying such as stricture or achalasia
- Inability to stand or sit upright for at least 30 minutes
- Patients at increased risk of aspiration should not receive FOSAMAX oral solution.
- Hypersensitivity to any component of this product
- Hypocalcemia (see PRECAUTIONS, General)

WARNINGS

FOSAMAX, like other bisphosphonates, may cause local irritation of the upper gastrointestinal mucosa.

Esophageal adverse experiences, such as esophagitis, esophageal ulcers and esophageal erosions, occasionally with bleeding and rarely followed by esophageal stricture or perforation, have been reported in patients receiving treatment with FOSAMAX. In some cases these have been severe and required hospitalization. Physicians should therefore be alert to any signs or symptoms signaling a possible esophageal reaction and patients should be instructed to discontinue FOSAMAX and seek medical attention if they develop dysphagia, odynophagia, retrosternal pain or new or worsening heartburn.

The risk of severe esophageal adverse experiences appears to be greater in patients who lie down after taking FOSAMAX and/or who fail to swallow it with the recommended amount of water, and/or who continue to take FOSAMAX after developing symptoms suggestive of esophageal irritation. Therefore, it is very important that the full dosing instructions are provided to, and understood by, the patient (see DOSAGE AND ADMINISTRATION). In patients who cannot comply with dosing instructions due to mental disability, therapy with FOSAMAX should be used under appropriate supervision.

Because of possible irritant effects of FOSAMAX on the upper gastrointestinal mucosa and a potential for worsening of the underlying disease, caution should be used when FOSAMAX is given to patients with active upper gastrointestinal problems (such as dysphagia, esophageal diseases, gastritis, duodenitis, or ulcers).

There have been post-marketing reports of gastric and duodenal ulcers, some severe and with complications, although no increased risk was observed in controlled clinical trials.

PRECAUTIONS

General

Causes of osteoporosis other than estrogen deficiency, aging, and glucocorticoid use should be considered.

Hypocalcemia must be corrected before initiating therapy with FOSAMAX (see CONTRAINDICATIONS). Other disorders affecting mineral metabolism (such as vitamin D deficiency) should also be effectively treated. In patients with these conditions, serum calcium and symptoms of hypocalcemia should be monitored during therapy with FOSAMAX.

Presumably due to the effects of FOSAMAX on increasing bone mineral, small, asymptomatic decreases in serum calcium and phosphate may occur, especially in patients with Paget's disease, in whom the pretreatment rate of bone turnover may be greatly elevated and in patients receiving glucocorticoids, in whom calcium absorption may be decreased.

Ensuring adequate calcium and vitamin D intake is especially important in patients with Paget's disease of bone and in patients receiving glucocorticoids.

Musculoskeletal Pain

In post marketing experience, severe and occasionally incapacitating bone, joint, and/or muscle pain has been reported in patients taking bisphosphonates that are approved for the prevention and treatment of osteoporosis (see ADVERSE REACTIONS). However, such reports have been infrequent. This category of drugs includes FOSAMAX (alendronate). Most of the patients were postmenopausal women. The time to onset of symptoms varied from one day to several months after starting the drug. Discontinue use if severe symptoms develop. Most patients had relief of symptoms after stopping. A subset had recurrence of symptoms when rechallenged with the same drug or another bisphosphonate.

In placebo-controlled clinical studies of FOSAMAX, the percentages of patients with these symptoms were similar in the FOSAMAX and placebo groups.

Dental

Osteonecrosis of the jaw, generally associated with tooth extraction and/or local infection, often with delayed healing, has been reported in patients taking bisphosphonates. Most reported cases of bisphosphonate-associated osteonecrosis have been in cancer patients treated with intravenous bisphosphonates, but some have occurred in patients with postmenopausal osteoporosis. Known risk factors for osteonecrosis include a diagnosis of cancer, concomitant therapies (e.g., chemotherapy, radiotherapy, corticosteroids), poor oral hygiene, and co-morbid disorders (e.g., pre-existing dental disease, anemia, coagulopathy, infection).

Patients who develop osteonecrosis of the jaw (ONJ) while on bisphosphonate therapy should receive care by an oral surgeon. Dental surgery may exacerbate the condition. For patients requiring dental procedures, there are no data available to suggest whether discontinuation of bisphosphonate treatment reduces the risk for ONJ. Clinical judgment of the treating physician should guide the management plan of each patient based on individual benefit/risk assessment.

Renal insufficency

FOSAMAX is not recommended for patients with renal insufficiency (creatinine clearance less than 35 mL/min). (See DOSAGE AND ADMINISTRATION.)

Glucocorticoid-induced osteoporosis

The risk versus benefit of FOSAMAX for treatment at daily dosages of glucocorticoids less than 7.5 mg of prednisone or equivalent has not been established (see INDICATIONS AND USAGE). Before initiating treatment, the hormonal status of both men and women should be ascertained and appropriate replacement considered.

A bone mineral density measurement should be made at the initiation of therapy and repeated after 6 to 12 months of combined FOSAMAX and glucocorticoid treatment.

The efficacy of FOSAMAX for the treatment of glucocorticoid-induced osteoporosis has been shown in patients with a median bone mineral density which was 1.2 standard deviations below the mean for healthy young adults.

The efficacy of FOSAMAX has been established in studies of two years' duration. The greatest increase in bone mineral density occurred in the first year with maintenance or smaller gains during the second year. Efficacy of FOSAMAX beyond two years has not been studied.

The efficacy of FOSAMAX in respect to fracture prevention has been demonstrated for vertebral fractures. However, this finding was based on very few fractures that occurred primarily in postmenopausal women. The efficacy for prevention of non-vertebral fractures has not been demonstrated.

Information for Patients General

Physicians should instruct their patients to read the patient package insert before starting therapy with FOSAMAX and to reread it each time the prescription is renewed.

Patients should be instructed to take supplemental calcium and vitamin D, if daily dietary intake is inadequate. Weight-bearing exercise should be considered along with the modification of certain behavioral factors, such as cigarette smoking and/or excessive alcohol consumption, if these factors exist.

Dosing Instructions

Patients should be instructed that the expected benefits of FOSAMAX may only be obtained when it is taken with plain water the first thing upon arising for the day at least 30 minutes before the first food, beverage, or medication of the day. Even dosing with orange juice or coffee has been shown to markedly reduce the absorption of FOSAMAX (see CLINICAL PHARMACOLOGY, Pharmacokinetics, Absorption).

To facilitate delivery to the stomach and thus reduce the potential for esophageal irritation patients should be instructed to swallow each tablet of FOSAMAX with a full glass of water (6-8 oz). To facilitate gastric emptying patients should drink at least 2 oz (a quarter of a cup) of water after taking FOSAMAX oral solution. Patients should be instructed not to lie down for at least 30 minutes and until after their first food of the day. Patients should not chew or suck on the tablet because of a potential for oropharyngeal ulceration. Patients should be specifically instructed not to take FOSAMAX at bedtime or before arising for the day. Patients should be informed that failure to follow these instructions may increase their risk of esophageal problems. Patients should be instructed that if they develop symptoms of esophageal disease (such as difficulty or pain upon swallowing, retrosternal pain or new or worsening heartburn) they should stop taking FOSAMAX and consult their physician.

Patients should be instructed that if they miss a dose of once weekly FOSAMAX, they should take one dose on the morning after they remember. They should not take two doses on the same day but should return to taking one dose once a week, as originally scheduled on their chosen day.

Drug Interactions

(also see CLINICAL PHARMACOLOGY, Pharmacokinetics, Drug Interactions)

Estrogen/hormone replacement therapy (HRT)

Concomitant use of HRT (estrogen ± progestin) and FOSAMAX was assessed in two clinical studies of one or two years' duration in postmenopausal osteoporotic women. In these studies, the safety and tolerability profile of the combination was consistent with those of the individual treatments; however, the degree of suppression of bone turnover (as assessed by mineralizing surface) was significantly greater with the combination than with either component alone. The long-term effects of combined FOSAMAX and HRT on fracture occurrence have not been studied (see CLINICAL PHARMACOLOGY, Clinical Studies, Concomitant use with estrogen/hormone replacement therapy (HRT) and ADVERSE REACTIONS, Clinical Studies, Concomitant use with estrogen/hormone replacement therapy).

Calcium Supplements/Antacids

It is likely that calcium supplements, antacids, and some oral medications will interfere with absorption of FOSAMAX. Therefore, patients must wait at least one-half hour after taking FOSAMAX before taking any other oral medications.

Aspirin

In clinical studies, the incidence of upper gastrointestinal adverse events was increased in patients receiving concomitant therapy with daily doses of FOSAMAX greater than 10 mg and aspirin-containing products.

Nonsteroidal Anti-inflammatory Drugs (NSAIDs)

FOSAMAX may be administered to patients taking NSAIDs. In a 3-year, controlled, clinical study (n=2027) during which a majority of patients received concomitant NSAIDs, the incidence of upper gastrointestinal adverse events was similar in patients taking FOSAMAX 5 or 10 mg/day compared to those taking placebo. However, since NSAID use is associated with gastrointestinal irritation, caution should be used during concomitant use with FOSAMAX.

Carcinogenesis, Mutagenesis, Impairment of Fertility

Harderian gland (a retro-orbital gland not present in humans) adenomas were increased in high-dose female mice (p=0.003) in a 92-week oral carcinogenicity study at doses of alendronate of 1, 3, and 10 mg/kg/day (males) or 1, 2, and 5 mg/kg/day (females). These doses are equivalent to 0.12 to 1.2 times a maximum recommended daily dose of 40 mg (Paget's disease) based on surface area, mg/m^2. The relevance of this finding to humans is unknown.

Parafollicular cell (thyroid) adenomas were increased in high-dose male rats (p=0.003) in a 2-year oral carcinogenicity study at doses of 1 and 3.75 mg/kg body weight. These doses are equivalent to 0.26 and 1 times a 40 mg human daily dose based on surface area, mg/m^2. The relevance of this finding to humans is unknown.

Alendronate was not genotoxic in the in vitro microbial mutagenesis assay with and without metabolic activation, in an in vitro mammalian cell mutagenesis assay, in an in vitro alkaline elution assay in rat hepatocytes, and in an in vivo chromosomal aberration assay in mice. In an in vitro chromosomal aberration assay in Chinese hamster ovary cells, however, alendronate gave equivocal results.

Alendronate had no effect on fertility (male or female) in rats at oral doses up to 5 mg/kg/day (1.3 times a 40 mg human daily dose based on surface area, mg/m^2).

Pregnancy Pregnancy Category C:

Reproduction studies in rats showed decreased postimplantation survival at 2 mg/kg/day and decreased body weight gain in normal pups at 1 mg/kg/day. Sites of incomplete fetal ossification were statistically significantly increased in rats beginning at 10 mg/kg/day in vertebral (cervical, thoracic, and lumbar), skull, and sternebral bones. The above doses ranged from 0.26 times (1 mg/kg) to 2.6 times (10 mg/kg) a maximum recommended daily dose of 40 mg (Paget's disease) based on surface area, mg/m^2. No similar fetal effects were seen when pregnant rabbits were treated at doses up to 35 mg/kg/day (10.3 times a 40 mg human daily dose based on surface area, mg/m^2).

Both total and ionized calcium decreased in pregnant rats at 15 mg/kg/day (3.9 times a 40 mg human daily dose based on surface area, mg/m^2) resulting in delays and failures of delivery. Protracted parturition due to maternal hypocalcemia occurred in rats at doses as low as 0.5 mg/kg/day (0.13 times a 40 mg human daily dose based on surface area, mg/m^2) when rats were treated from before mating through gestation. Maternotoxicity (late pregnancy deaths) occurred in the female rats treated with 15 mg/kg/day for varying periods of time ranging from treatment only during pre-mating to treatment only during early, middle, or late gestation; these deaths were lessened but not eliminated by cessation of treatment. Calcium supplementation either in the drinking water or by minipump could not ameliorate the hypocalcemia or prevent maternal and neonatal deaths due to delays in delivery; calcium supplementation IV prevented maternal, but not fetal deaths.

Bisphosphonates are incorporated into the bone matrix, from which they are gradually released over a period of years. The amount of bisphosphonate incorporated into adult bone, and hence, the amount available for release back into the systemic circulation, is directly related to the dose and duration of bisphosphonate use. There are no data on fetal risk in humans. However, there is a theoretical risk of fetal harm, predominantly skeletal, if a woman becomes pregnant after completing a course of bisphosphonate therapy. The impact of variables such as time between cessation of bisphosphonate therapy to conception, the particular bisphosphonate used, and the route of administration (intravenous versus oral) on the risk has not been studied.

There are no studies in pregnant women. FOSAMAX should be used during pregnancy only if the potential benefit justifies the potential risk to the mother and fetus.

Nursing Mothers

It is not known whether alendronate is excreted in human milk. Because many drugs are excreted in human milk, caution should be exercised when FOSAMAX is administered to nursing women.

Pediatric Use

The efficacy and safety of FOSAMAX were examined in a randomized, double-blind, placebo-controlled two-year study of 139 pediatric patients, aged 4-18 years, with severe osteogenesis imperfecta. One-hundred-and-nine patients were randomized to 5 mg FOSAMAX daily (weight less than 40 kg) or 10 mg FOSAMAX daily (weight greater than or equal to 40 kg) and 30 patients to placebo. The mean baseline lumbar spine BMD Z-score of the patients was -4.5. The mean change in lumbar spine BMD Z-score from baseline to Month 24 was 1.3 in the FOSAMAX-treated patients and 0.1 in the placebo-treated patients. Treatment with FOSAMAX did not reduce the risk of fracture. Sixteen percent of the FOSAMAX patients who sustained a radiologically-confirmed fracture by Month 12 of the study had delayed fracture healing (callus remodeling) or fracture non-union when assessed radiographically at Month 24 compared with 9% of the placebo-treated patients. In FOSAMAX-treated patients, bone histomorphometry data obtained at Month 24 demonstrated decreased bone turnover and delayed mineralization time; however, there were no mineralization defects. There were no statistically significant differences between the FOSAMAX and placebo groups in reduction of bone pain.

FOSAMAX is not indicated for use in children.

(For clinical adverse experiences in children, see ADVERSE REACTIONS, Clinical Studies, Osteogenesis Imperfecta.)

Geriatric Use

Of the patients receiving FOSAMAX in the Fracture Intervention Trial (FIT), 71% (n=2302) were greater than or equal to 65 years of age and 17% (n=550) were greater than or equal to 75 years of age. Of the patients receiving FOSAMAX in the United States and Multinational osteoporosis treatment studies in women, osteoporosis studies in men, glucocorticoid-induced osteoporosis studies, and Paget's disease studies (see CLINICAL PHARMACOLOGY, Clinical Studies), 45%, 54%, 37%, and 70%, respectively, were 65 years of age or over. No overall differences in efficacy or safety were observed between these patients and younger patients, but greater sensitivity of some older individuals cannot be ruled out.

ADVERSE REACTIONS

Clinical Studies

In clinical studies of up to five years in duration adverse experiences associated with FOSAMAX usually were mild, and generally did not require discontinuation of therapy.

FOSAMAX has been evaluated for safety in approximately 8000 postmenopausal women in clinical studies.

Treatment of osteoporosis Postmenopausal women

In two identically designed, three-year, placebo-controlled, double-blind, multicenter studies (United States and Multinational; n=994), discontinuation of therapy due to any clinical adverse experience occurred in 4.1% of 196 patients treated with FOSAMAX 10 mg/day and 6.0% of 397 patients treated with placebo. In the Fracture Intervention Trial (n=6459), discontinuation of therapy due to any clinical adverse experience occurred in 9.1% of 3236 patients treated with FOSAMAX 5 mg/day for 2 years and 10 mg/day for either one or two additional years and 10.1% of 3223 patients treated with placebo. Discontinuations due to upper gastrointestinal adverse experiences were: FOSAMAX, 3.2%; placebo, 2.7%. In these study populations, 49-54% had a history of gastrointestinal disorders at baseline and 54-89% used nonsteroidal anti-inflammatory drugs or aspirin at some time during the studies. Adverse experiences from these studies considered by the investigators as possibly, probably, or definitely drug related in ≥1% of patients treated with either FOSAMAX or placebo are presented in the following table.

Osteoporosis Treatment Studies in Postmenopausal Women: Adverse Experiences Considered Possibly, Probably, or Definitely Drug Related by the Investigators and Reported in ≥1% of Patients
 | United States/ Studies | Multinational | Fracture Trial | Intervention
 | FOSAMAX* % (n=196) | Placebo % (n=397) | FOSAMAX† % (n=3236) | Placebo % (n=3223)
Gastrointestinal
abdominal pain | 6.6 | 4.8 | 1.5 | 1.5
nausea | 3.6 | 4.0 | 1.1 | 1.5
dyspepsia | 3.6 | 3.5 | 1.1 | 1.2
constipation | 3.1 | 1.8 | 0.0 | 0.2
diarrhea | 3.1 | 1.8 | 0.6 | 0.3
flatulence | 2.6 | 0.5 | 0.2 | 0.3
acid regurgitation | 2.0 | 4.3 | 1.1 | 0.9
esophageal ulcer | 1.5 | 00 | 0.1 | 0.1
vomiting | 1.0 | 1.5 | 0.2 | 0.3
dysphagia | 1.0 | 0.0 | 0.1 | 0.1
abdominal distention | 1.0 | 0.8 | 0.0 | 0.0
gastritis | 0.5 | 1.3 | 0.6 | 0.7
Musculoskeletal
musculoskeletal (bone, muscle or joint) pain | 4.1 | 2.5 | 0.4 | 0.3
muscle cram | 0.0 | 1.0 | 0.2 | 0.1
Nervous System/Psychiatric
headache | 2.6 | 1.5 | 0.2 | 0.2
dizziness | 0.0 | 1.0 | 0.0 | 0.1
Special Senses
taste perversion | 0.5 | 1.0 | 0.1 | 0.0

* 10 mg/day for three years
† 5 mg/day for 2 years and 10 mg/day for either 1 or 2 additional years

Rarely, rash and erythema have occurred.

One patient treated with FOSAMAX (10 mg/day), who had a history of peptic ulcer disease and gastrectomy and who was taking concomitant aspirin developed an anastomotic ulcer with mild hemorrhage, which was considered drug related. Aspirin and FOSAMAX were discontinued and the patient recovered.

The adverse experience profile was similar for the 401 patients treated with either 5 or 20 mg doses of FOSAMAX in the United States and Multinational studies. The adverse experience profile for the 296 patients who received continued treatment with either 5 or 10 mg doses of FOSAMAX in the two-year extension of these studies (treatment years 4 and 5) was similar to that observed during the three-year placebo-controlled period. During the extension period, of the 151 patients treated with FOSAMAX 10 mg/day, the proportion of patients who discontinued therapy due to any clinical adverse experience was similar to that during the first three years of the study.

In a one-year, double-blind, multicenter study, the overall safety and tolerability profiles of once weekly FOSAMAX 70 mg and FOSAMAX 10 mg daily were similar. The adverse experiences considered by the investigators as possibly, probably, or definitely drug related in ≥1% of patients in either treatment group are presented in the following

table.

Osteoporosis Treatment Studies in Postmenopausal Women: Adverse Experiences Considered Possibly, Probably, or Definitely Drug Related by the Investigators and Reported in ≥1% of Patients
 | Once Weekly FOSAMAX 70 mg % (n=519) | FOSAMAX 10 mg/day % (n=370)
Gastrointestinal abdominal pain dyspepsia acid regurgitation nausea abdominal distention constipation flatulence gastritis gastric ulcer | 3.7 2.7 1.9 1.9 1.0 0.8 0.4 0.2 0.0 | 3.0 2.2 2.4 2.4 1.4 1.6 1.6 1.1 1.1
Musculoskeletal musculoskeletal (bone, muscle, joint) pain muscle cramp | 2.9 0.2 | 3.2 1.1

Men

In two placebo-controlled, double-blind, multicenter studies in men (a two-year study of FOSAMAX 10 mg/day and a one-year study of once weekly FOSAMAX 70 mg) the rates of discontinuation of therapy due to any clinical adverse experience were 2.7% for FOSAMAX 10 mg/day vs. 10.5% for placebo, and 6.4% for once weekly FOSAMAX 70 mg vs. 8.6% for placebo. The adverse experiences considered by the investigators as possibly, probably, or definitely drug related in ≥2% of patients treated with either FOSAMAX or placebo are presented in the following table.

Osteoporosis Studies in Men: Adverse Experiences Considered Possibly, Probably, or Definitely Drug Related by the Investigators and Reported in ≥2% of Patients
 | Two-year Study | One-year Study
 | FOSAMAX 10 mg/day % (n=146) | Placebo % (n=95) | Once Weekly FOSAMAX 70 mg % (n=109) | Placebo % (n=58)
Gastrointestinal acid regurgitation flatulence gastroesophageal reflux disease dyspepsia diarrhea abdominal pain nausea | 4.1 4.1 0.7 3.4 1.4 2.1 2.1 | 3.2 1.1 3.2 0.0 1.1 1.1 0.0 | 0.0 0.0 2.8 2.8 2.8 0.9 0.0 | 0.0 0.0 0.0 1.7 0.0 3.4 0.0

Prevention of osteoporosis in postmenopausal women

The safety of FOSAMAX 5 mg/day in postmenopausal women 40-60 years of age has been evaluated in three double-blind, placebo-controlled studies involving over 1,400 patients randomized to receive FOSAMAX for either two or three years. In these studies the overall safety profiles of FOSAMAX 5 mg/day and placebo were similar. Discontinuation of therapy due to any clinical adverse experience occurred in 7.5% of 642 patients treated with FOSAMAX 5 mg/day and 5.7% of 648 patients treated with placebo.

In a one-year, double-blind, multicenter study, the overall safety and tolerability profiles of once weekly FOSAMAX 35 mg and FOSAMAX 5 mg daily were similar.

The adverse experiences from these studies considered by the investigators as possibly, probably, or definitely drug related in ≥1% of patients treated with either once weekly FOSAMAX 35 mg, FOSAMAX 5 mg/day or placebo are presented in the following table.

Osteoporosis Prevention Studies in Postmenopausal Women: Adverse Experiences Considered Possibly, Probably, or Definitely Drug Related by the Investigators and Reported in ≥1% of Patients
 | Two/Three-Year Studies | One-Year Study
 | FOSAMAX 5 mg/day % (n=642) | Placebo % (n=648) | FOSAMAX 5 mg/day % (n=361) | Once Weekly FOSAMAX 35 mg % (n=362)
Gastrointestinal dyspepsia abdominal pain acid regurgitation nausea diarrhea constipation abdominal distention | 1.9 1.7 1.4 1.4 1.1 0.9 0.2 | 1.4 3.4 2.5 1.4 1.7 0.5 0.3 | 2.2 4.2 4.2 2.5 1.1 1.7 1.4 | 1.7 2.2 4.7 1.4 0.6 0.3 1.1
Musculoskeletal musculoskeletal (bone, muscle or joint) pain | 0.8 | 0.9 | 1.9 | 2.2

Concomitant use with estrogen/hormone replacement therapy

In two studies (of one and two years' duration) of postmenopausal osteoporotic women (total: n=853), the safety and tolerability profile of combined treatment with FOSAMAX 10 mg once daily and estrogen ± progestin (n=354) was consistent with those of the individual treatments.

Treatment of glucocorticoid-induced osteoporosis

In two, one-year, placebo-controlled, double-blind, multicenter studies in patients receiving glucocorticoid treatment, the overall safety and tolerability profiles of FOSAMAX 5 and 10 mg/day were generally similar to that of placebo. The adverse experiences considered by the investigators as possibly, probably, or definitely drug related in ≥1% of patients treated with either FOSAMAX 5 or 10 mg/day or placebo are presented in the following table.

One-Year Studies in Glucocorticoid-Treated Patients: Adverse Experiences Considered Possibly, Probably, or Definitely Drug Related by the Investigators and Reported in ≥1% of Patients
 | FOSAMAX 10 mg/day % (n=157) | FOSAMAX 5 mg/day % (n=161) | Placebo % (n=159)
Gastrointestinal abdominal pain acid regurgitation constipation melena nausea diarrhea Nervous System/Psychiatric headache | 3.2 2.5 1.3 1.3 0.6 0.0 0.6 | 1.9 1.9 0.6 0.0 1.2 0.0 0.0 | 0.0 1.3 0.0 0.0 0.6 1.3 1.3

The overall safety and tolerability profile in the glucocorticoid-induced osteoporosis population that continued therapy for the second year of the studies (FOSAMAX: n=147) was consistent with that observed in the first year.

Paget's disease of bone

In clinical studies (osteoporosis and Paget's disease), adverse experiences reported in 175 patients taking FOSAMAX 40 mg/day for 3-12 months were similar to those in postmenopausal women treated with FOSAMAX 10 mg/day. However, there was an apparent increased incidence of upper gastrointestinal adverse experiences in patients taking FOSAMAX 40 mg/day (17.7% FOSAMAX vs. 10.2% placebo). One case of esophagitis and two cases of gastritis resulted in discontinuation of treatment.

Additionally, musculoskeletal (bone, muscle or joint) pain, which has been described in patients with Paget's disease treated with other bisphosphonates, was considered by the investigators as possibly, probably, or definitely drug related in approximately 6% of patients treated with FOSAMAX 40 mg/day versus approximately 1% of patients treated with placebo, but rarely resulted in discontinuation of therapy. Discontinuation of therapy due to any clinical adverse experience occurred in 6.4% of patients with Paget's disease treated with FOSAMAX 40 mg/day and 2.4% of patients treated with placebo.

Osteogenesis Imperfecta

FOSAMAX is not indicated for use in children.

The overall safety profile of FOSAMAX in OI patients treated for up to 24 months was generally similar to that of adults with osteoporosis treated with FOSAMAX. However, there was an increased occurrence of vomiting in OI patients treated with FOSAMAX compared to placebo. During the 24-month treatment period, vomiting was observed in 32 of 109 (29.4%) patients treated with FOSAMAX and 3 of 30 (10%) patients treated with placebo.

In a pharmacokinetic study, 6 of 24 pediatric OI patients who received a single oral dose of FOSAMAX 35 or 70 mg developed fever, flu-like symptoms, and/or mild lymphocytopenia within 24 to 48 hours after administration. These events, lasting no more than 2 to 3 days and responding to acetaminophen, are consistent with an acute-phase response that has been reported in patients receiving bisphosphonates, including FOSAMAX. See ADVERSE REACTIONS, Post-Marketing Experience, Body as a Whole.

Laboratory Test Findings

In double-blind, multicenter, controlled studies, asymptomatic, mild, and transient decreases in serum calcium and phosphate were observed in approximately 18% and 10%, respectively, of patients taking FOSAMAX versus approximately 12% and 3% of those taking placebo. However, the incidences of decreases in serum calcium to less than 8.0 mg/dL (2.0 mM) and serum phosphate to less than or equal to 2.0 mg/dL (0.65 mM) were similar in both treatment groups.

Post-Marketing Experience

The following adverse reactions have been reported in post-marketing use:

Body as a Whole: hypersensitivity reactions including urticaria and rarely angioedema. Transient symptoms of myalgia, malaise, asthenia and rarely, fever have been reported with FOSAMAX, typically in association with initiation of treatment. Rarely, symptomatic hypocalcemia has occurred, generally in association with predisposing conditions. Rarely, peripheral edema.

Gastrointestinal: esophagitis, esophageal erosions, esophageal ulcers, rarely esophageal stricture or perforation, and oropharyngeal ulceration. Gastric or duodenal ulcers, some severe and with complications have also been reported (see WARNINGS, PRECAUTIONS, Information for Patients, and DOSAGE AND ADMINISTRATION).

Localized osteonecrosis of the jaw, generally associated with tooth extraction and/or local infection, often with delayed healing, has been reported rarely (see PRECAUTIONS, Dental).

Musculoskeletal: bone, joint, and/or muscle pain, occasionally severe, and rarely incapacitating (see PRECAUTIONS, Musculoskeletal Pain); joint swelling.

Nervous system: dizziness and vertigo.

Skin: rash (occasionally with photosensitivity), pruritus, alopecia, rarely severe skin reactions, including Stevens-Johnson syndrome and toxic epidermal necrolysis.

Special Senses: rarely uveitis, scleritis or episcleritis.

OVERDOSAGE

Significant lethality after single oral doses was seen in female rats and mice at 552 mg/kg (3256 mg/m^2) and 966 mg/kg (2898 mg/m^2), respectively. In males, these values were slightly higher, 626 and 1280 mg/kg, respectively. There was no lethality in dogs at oral doses up to 200 mg/kg (4000 mg/m^2).

No specific information is available on the treatment of overdosage with FOSAMAX. Hypocalcemia, hypophosphatemia, and upper gastrointestinal adverse events, such as upset stomach, heartburn, esophagitis, gastritis, or ulcer, may result from oral overdosage. Milk or antacids should be given to bind alendronate. Due to the risk of esophageal irritation, vomiting should not be induced and the patient should remain fully upright.

Dialysis would not be beneficial.

DOSAGE AND ADMINISTRATION

FOSAMAX must be taken at least one-half hour before the first food, beverage, or medication of the day with plain water only (see PRECAUTIONS, Information for Patients). Other beverages (including mineral water), food, and some medications are likely to reduce the absorption of FOSAMAX (see PRECAUTIONS, Drug Interactions). Waiting less than 30 minutes, or taking FOSAMAX with food, beverages (other than plain water) or other medications will lessen the effect of FOSAMAX by decreasing its absorption into the body.

FOSAMAX should only be taken upon arising for the day. To facilitate delivery to the stomach and thus reduce the potential for esophageal irritation, a FOSAMAX tablet should be swallowed with a full glass of water (6-8 oz). To facilitate gastric emptying FOSAMAX oral solution should be followed by at least 2 oz (a quarter of a cup) of water. Patients should not lie down for at least 30 minutes and until after their first food of the day. FOSAMAX should not be taken at bedtime or before arising for the day. Failure to follow these instructions may increase the risk of esophageal adverse experiences (see WARNINGS, PRECAUTIONS, Information for Patients).

Patients should receive supplemental calcium and vitamin D, if dietary intake is inadequate (see PRECAUTIONS, General).

No dosage adjustment is necessary for the elderly or for patients with mild-to-moderate renal insufficiency (creatinine clearance 35 to 60 mL/min). FOSAMAX is not recommended for patients with more severe renal insufficiency (creatinine clearance less than 35 mL/min) due to lack of experience.

Treatment of osteoporosis in postmenopausal women

(see INDICATIONS AND USAGE)

The recommended dosage is:

- one 70 mg tablet once weekly
  or
- one bottle of 70 mg oral solution once weekly
  or
- one 10 mg tablet once daily

Treatment to increase bone mass in men with osteoporosis

The recommended dosage is:

- one 70 mg tablet once weekly
  or
- one bottle of 70 mg oral solution once weekly
  or
- one 10 mg tablet once daily

Prevention of osteoporosis in postmenopausal women

(see INDICATIONS AND USAGE)

The recommended dosage is:

- one 35 mg tablet once weekly
  or
- one 5 mg tablet once daily

The safety of treatment and prevention of osteoporosis with FOSAMAX has been studied for up to 7 years.

Treatment of glucocorticoid-induced osteoporosis in men and women

The recommended dosage is one 5 mg tablet once daily, except for postmenopausal women not receiving estrogen, for whom the recommended dosage is one 10 mg tablet once daily.

Paget's disease of bone in men and women

The recommended treatment regimen is 40 mg once a day for six months.

Retreatment of Paget's disease

In clinical studies in which patients were followed every six months, relapses during the 12 months following therapy occurred in 9% (3 out of 32) of patients who responded to treatment with FOSAMAX. Specific retreatment data are not available, although responses to FOSAMAX were similar in patients who had received prior bisphosphonate therapy and those who had not. Retreatment with FOSAMAX may be considered, following a six-month post-treatment evaluation period in patients who have relapsed, based on increases in serum alkaline phosphatase, which should be measured periodically. Retreatment may also be considered in those who failed to normalize their serum alkaline phosphatase.

HOW SUPPLIED

No. 3759 — Tablets FOSAMAX, 5 mg, are white, round, uncoated tablets with an outline of a bone image on one side and code MRK 925 on the other. They are supplied as follows:

NDC 54868-4384-0 bottles of 30.

No. 3797 — Tablets FOSAMAX, 10 mg, are white, oval, wax-polished tablets with code MRK on one side and 936 on the other. They are supplied as follows:

NDC 54868-3857-0 bottles of 30.

No. 3813 — Tablets FOSAMAX, 35 mg, are white, oval, uncoated tablets with code 77 on one side and a bone image on the other. They are supplied as follows:

NDC 54868-4463-0 bottle of 4.

No. 3814 — Tablets FOSAMAX, 70 mg, are white, oval, uncoated tablets with code 31 on one side and an outline of a bone image on the other. They are supplied as follows:

NDC 54868-4462-0 bottle of 4

NDC 54868-4462-1 bottle of 12.

Storage

FOSAMAX Tablets:

Store in a well-closed container at room temperature, 15-30°C (59-86°F).

FOSAMAX Oral Solution:

Store at 25°C (77°F), excursions permitted to 15-30°C (59-86°F). [See USP Controlled Room Temperature.] Do not freeze.

MERCK & CO., INC., Whitehouse Station, NJ 08889, USA

Issued February 2008

Printed in USA

9635608

9636808

SUPPLEMENTAL PATIENT MATERIAL

Patient Information

Once Weekly FOSAMAX® (FOSS-ah-max)

(alendronate sodium)

Tablets and Oral Solution

Read this information before you start taking FOSAMAX2. Also, read the leaflet each time you refill your prescription, just in case anything has changed. This leaflet does not take the place of discussions with your doctor. You and your doctor should discuss FOSAMAX when you start taking your medicine and at regular checkups.

2

Registered trademark of MERCK & CO., Inc.
COPYRIGHT © 2000 MERCK & CO., Inc.
All rights reserved

What is the most important information I should know about once weekly FOSAMAX?

- You must take once weekly FOSAMAX exactly as directed to help make sure it works and to help lower the chance of problems in your esophagus (the tube that connects your mouth and stomach). (See “ How should I take once weekly FOSAMAX?”).
- If you have chest pain, new or worsening heartburn, or have trouble or pain when you swallow, stop taking FOSAMAX and call your doctor. (See “ What are the possible side effects of FOSAMAX?”).

What is FOSAMAX?

FOSAMAX is a prescription medicine for:

- The treatment or prevention of osteoporosis (thinning of bone) in women after menopause. It reduces the chance of having a hip or spinal fracture (break).
- Treatment to increase bone mass in men with osteoporosis.
- FOSAMAX tablets are for treatment and prevention of osteoporosis.
- FOSAMAX oral solution is for treatment of osteoporosis.

Improvement in bone density may be observed as early as 3 months after you start taking FOSAMAX even though you won’t see or feel a difference. For FOSAMAX to continue to work, you need to keep taking it.

FOSAMAX is not a hormone.

There is more information about osteoporosis at the end of this leaflet.

Who should not take FOSAMAX?

Do not take FOSAMAX (tablets or oral solution) if you:

- Have certain problems with your esophagus, the tube that connects your mouth with your stomach
- Cannot stand or sit upright for at least 30 minutes
- Have low levels of calcium in your blood
- Are allergic to FOSAMAX or any of its ingredients. A list of ingredients is at the end of this leaflet.

Do not take FOSAMAX oral solution if you have trouble swallowing liquids.

What should I tell my doctor before using FOSAMAX?

Tell your doctor about all of your medical conditions, including if you:

- have problems with swallowing
- have stomach or digestive problems
- have kidney problems
- are pregnant or planning to become pregnant. It is not known if FOSAMAX can harm your unborn baby.
- are breastfeeding. It is not known if FOSAMAX passes into your milk and if it can harm your baby.

Tell your doctor about all medicines you take, including prescription and non-prescription medicines, vitamins, and herbal supplements.

Know the medicines you take. Keep a list of them and show it to your doctor and pharmacist each time you get a new medicine.

How should I take once weekly FOSAMAX?

- Choose the day of the week that best fits your schedule.
- Take 1 dose of FOSAMAX every week on your chosen day after you get up for the day and before taking your first food, drink, or other medicine
- Take FOSAMAX while you are sitting or standing.
- Take your FOSAMAX with plain water only as follows:
  - TABLETS: Swallow one tablet with a full glass (6-8 oz) of plain water.
  - ORAL SOLUTION: Drink one entire bottle of solution followed by at least 2 ounces (a quarter of a cup) of plain water.

Do not take FOSAMAX with:

Mineral water
Coffee or tea
Juice

FOSAMAX works only if it is taken on an empty stomach.

Do not chew or suck on a tablet of FOSAMAX.

After taking your FOSAMAX, wait at least 30 minutes:

- before you lie down. You may sit, stand or walk, and do normal activities like reading.
- before you take your first food or drink except for plain water.
- before you take other medicines, including antacids, calcium, and other supplements and vitamins.

Do not lie down until after your first food of the day.

- It is important that you keep taking FOSAMAX for as long as your doctor says to take it. For FOSAMAX to continue to work, you need to keep taking it.

What should I do if I miss a dose of FOSAMAX or if I take too many?

- If you miss a dose, take only 1 dose of FOSAMAX on the morning after you remember. Do not take 2 doses on the same day. Continue your usual schedule of 1 dose once a week on your chosen day.
- If you think you took more than the prescribed dose of FOSAMAX, drink a full glass of milk and call your doctor right away. Do not try to vomit. Do not lie down.

What should I avoid while taking FOSAMAX?

- Do not eat, drink, or take other medicines or supplements before taking FOSAMAX.
- Wait for at least 30 minutes after taking FOSAMAX to eat, drink, or take other medicines or supplements.
- Do not lie down for at least 30 minutes after taking FOSAMAX. Do not lie down until after your first food of the day.

What are the possible side effects of FOSAMAX?

FOSAMAX may cause problems in your esophagus (the tube that connects the mouth and stomach). (See “ What is the most important information I should know about once weekly FOSAMAX?”.) These problems include irritation, inflammation, or ulcers of the esophagus, which may sometimes bleed. This may occur especially if you do not drink a full glass of water with FOSAMAX or if you lie down in less than 30 minutes or before your first food of the day.

- Stop taking FOSAMAX and call your doctor right away if you get any of these signs of possible serious problems of the esophagus:
  - Chest pain
  - New or worsening heartburn
  - Trouble or pain when swallowing
- Esophagus problems may get worse if you continue to take FOSAMAX.
- Mouth sores (ulcers) may occur if the FOSAMAX tablet is chewed or dissolved in the mouth.
- You may get flu-like symptoms, typically at the start of treatment with FOSAMAX.
- You may get allergic reactions, such as hives or, in rare cases, swelling of your face, lips, tongue, or throat.
- FOSAMAX may cause jaw-bone problems in some people. Jaw-bone problems may include infection, and delayed healing after teeth are pulled.
- The most common side effect is stomach area (abdominal) pain. Less common side effects are nausea, vomiting, a full or bloated feeling in the stomach, constipation, diarrhea, black or bloody stools (bowel movements), gas, eye pain, rash that may be made worse by sunlight, hair loss, headache, dizziness, a changed sense of taste, joint swelling or swelling in the hands or legs, and bone, muscle, or joint pain.
- Call your doctor if you develop severe bone, muscle, or joint pain.

Tell your doctor about any side effect that bothers you or that does not go away.

These are not all the side effects with FOSAMAX. Ask your doctor or pharmacist for more information.

How do I store FOSAMAX?

- Store at room temperature, 59 to 86°F (15 to 30°C).
- Safely discard FOSAMAX that is out-of-date or no longer needed.
- Keep FOSAMAX and all medicines out of the reach of children.

General information about using FOSAMAX safely and effectively

Medicines are sometimes prescribed for conditions that are not mentioned in patient information leaflets. Do not use FOSAMAX for a condition for which it was not prescribed. Do not give FOSAMAX to other people, even if they have the same symptoms you have. It may harm them.

FOSAMAX is not indicated for use in children.

This leaflet is a summary of information about FOSAMAX. If you have any questions or concerns about FOSAMAX or osteoporosis, talk to your doctor, pharmacist, or other health care provider. You can ask your doctor or pharmacist for information about FOSAMAX written for health care providers. For more information, call 1-877-408-4699 (toll-free) or visit the following website: www.fosamax.com.

What are the ingredients in FOSAMAX?

Tablets
FOSAMAX tablets contain alendronate sodium as the active ingredient and the following inactive ingredients: cellulose, lactose, croscarmellose sodium and magnesium stearate.

Oral Solution
Fosamax oral solution contains alendronate sodium as the active ingredient and the following inactive ingredients: sodium citrate, citric acid, sodium saccharin, artificial raspberry flavor, purified water, sodium propylparaben and sodium butylparaben.

What should I know about osteoporosis?

Normally your bones are being rebuilt all the time. First, old bone is removed (resorbed). Then a similar amount of new bone is formed. This balanced process keeps your skeleton healthy and strong.

Osteoporosis is a thinning and weakening of the bones. It is common in women after menopause, and may also occur in men. In osteoporosis, bone is removed faster than it is formed, so overall bone mass is lost and bones become weaker. Therefore, keeping bone mass is important to keep your bones healthy. In both men and women, osteoporosis may also be caused by certain medicines called corticosteroids.

At first, osteoporosis usually has no symptoms, but it can cause fractures (broken bones). Fractures usually cause pain. Fractures of the bones of the spine may not be painful, but over time they can make you shorter. Eventually, your spine can curve and your body can become bent over. Fractures may happen during normal, everyday activity, such as lifting, or from minor injury that would normally not cause bones to break. Fractures most often occur at the hip, spine, or wrist. This can lead to pain, severe disability, or loss of ability to move around (mobility).

Who is at risk for osteoporosis?

Many things put people at risk of osteoporosis. The following people have a higher chance of getting osteoporosis:

Women who:

- Are going through or who are past menopause

Men who:

- Are elderly

People who:

- Are white (Caucasian) or oriental (Asian)
- Are thin
- Have family member with osteoporosis
- Do not get enough calcium or vitamin D
- Do not exercise
- Smoke
- Drink alcohol often
- Take bone thinning medicines (like prednisone or other corticosteroids) for a long time

What can I do to help prevent or treat osteoporosis?

In addition to FOSAMAX, your doctor may suggest one or more of the following lifestyle changes:

- Stop smoking. Smoking may increase your chance of getting osteoporosis.
- Reduce the use of alcohol. Too much alcohol may increase the risk of osteoporosis and injuries that can cause fractures.
- Exercise regularly. Like muscles, bones need exercise to stay strong and healthy. Exercise must be safe to prevent injuries, including fractures. Talk with your doctor before you begin any exercise program.
- Eat a balanced diet. Having enough calcium in your diet is important. Your doctor can advise you whether you need to change your diet or take any dietary supplements, such as calcium or vitamin D.

Rx only

MERCK & CO., INC.
Whitehouse Station, NJ 08889, USA

Issued February 2008

9635608

Patient Information

FOSAMAX® (FOSS-ah-max)

(alendronate sodium) Tablets

Read this information before you start taking FOSAMAX3. Also, read the leaflet each time you refill your prescription, just in case anything has changed. This leaflet does not take the place of discussions with your doctor. You and your doctor should discuss FOSAMAX when you start taking your medicine and at regular checkups.

3

Registered trademark of MERCK & CO., Inc.
COPYRIGHT © 1995, 1997, 2000 MERCK & CO., Inc.
All rights reserved

What is the most important information I should know about FOSAMAX?

- You must take FOSAMAX exactly as directed to help make sure it works and to help lower the chance of problems in your esophagus (the tube that connects your mouth and stomach). (See “ How should I take FOSAMAX?”).
- If you have chest pain, new or worsening heartburn, or have trouble or pain when you swallow, stop taking FOSAMAX and call your doctor. (See “ What are the possible side effects of FOSAMAX?”).

What is FOSAMAX?

FOSAMAX is a prescription medicine for:

- The treatment or prevention of osteoporosis (thinning of bone) in women after menopause. It reduces the chance of having a hip or spinal fracture (break).
- Treatment to increase bone mass in men with osteoporosis.
- The treatment of osteoporosis in either men or women who are taking corticosteroid medicines (for example, prednisone).

Improvement in bone density may be observed as early as 3 months after you start taking FOSAMAX even though you won’t see or feel a difference. For FOSAMAX to continue to work, you need to keep taking it.

FOSAMAX is not a hormone.

There is more information about osteoporosis at the end of this leaflet.

Who should not take FOSAMAX?

Do not take FOSAMAX if you:

- Have certain problems with your esophagus, the tube that connects your mouth with your stomach
- Cannot stand or sit upright for at least 30 minutes
- Have low levels of calcium in your blood
- Are allergic to FOSAMAX or any of its ingredients. A list of ingredients is at the end of this leaflet.

What should I tell my doctor before using FOSAMAX?

Tell your doctor about all of your medical conditions, including if you:

- have problems with swallowing
- have stomach or digestive problems
- have kidney problems
- are pregnant or planning to become pregnant. It is not known if FOSAMAX can harm your unborn baby.
- are breastfeeding. It is not known if FOSAMAX passes into your milk and if it can harm your baby.

Tell your doctor about all medicines you take, including prescription and non-prescription medicines, vitamins, and herbal supplements.

Know the medicines you take. Keep a list of them and show it to your doctor and pharmacist each time you get a new medicine.

How should I take FOSAMAX?

- Take 1 FOSAMAX tablet once a day, every day after you get up for the day and before taking your first food, drink, or other medicine.
- Take FOSAMAX while you are sitting or standing.
- Swallow your FOSAMAX tablet with a full glass (6-8 oz) of plain water only.

Do not take FOSAMAX with:

Mineral water
Coffee or tea
Juice

FOSAMAX works only if taken on an empty stomach.

Do not chew or suck on a tablet of FOSAMAX.

After swallowing your FOSAMAX tablet, wait at least 30 minutes:

- before you lie down. You may sit, stand or walk, and do normal activities like reading.
- before you take your first food or drink except for plain water.
- before you take other medicines, including antacids, calcium, and other supplements and vitamins.

Do not lie down until after first food of the day.

- It is important that you keep taking FOSAMAX for as long as your doctor says to take it. For FOSAMAX to continue to work, you need to keep taking it.

What should I do if I miss a dose of FOSAMAX or if I take too many?

- If you miss a dose, do not take it later in the day. Continue your usual schedule of 1 tablet once a day the next morning.
- If you think you took more than the prescribed dose of FOSAMAX, drink a full glass of milk and call your doctor right away. Do not try to vomit. Do not lie down.

What should I avoid while taking FOSAMAX?

- Do not eat, drink, or take other medicines or supplements before taking FOSAMAX.
- Wait for at least 30 minutes after taking FOSAMAX to eat, drink, or take other medicines or supplements.
- Do not lie down for at least 30 minutes after taking FOSAMAX. Do not lie down until after your first food of the day.

What are the possible side effects of FOSAMAX?

FOSAMAX may cause problems in your esophagus (the tube that connects the mouth and stomach). (See “ What is the most important information I should know about FOSAMAX?”.) These problems include irritation, inflammation, or ulcers of the esophagus, which may sometimes bleed. This may occur especially if you do not drink a full glass of water with FOSAMAX or if you lie down in less than 30 minutes or before your first food of the day.

- Stop taking FOSAMAX and call your doctor right away if you get any of these signs of possible serious problems of the esophagus:
  - Chest pain
  - New or worsening heartburn
  - Trouble or pain when swallowing
- Esophagus problems may get worse if you continue to take FOSAMAX.
- Mouth sores (ulcers) may occur if the FOSAMAX tablet is chewed or dissolved in the mouth.
- You may get flu-like symptoms typically at the start of treatment with FOSAMAX.
- You may get allergic reactions, such as hives or, in rare cases, swelling of your face, lips, tongue, or throat.
- FOSAMAX may cause jaw-bone problems in some people. Jaw-bone problems include infection, and delayed healing after teeth are pulled.
- The most common side effect is stomach area (abdominal) pain. Less common side effects are nausea, vomiting, a full or bloated feeling in the stomach, constipation, diarrhea, black or bloody stools (bowel movements), gas, eye pain, rash that may be made worse by sunlight, hair loss, headache, dizziness, a changed sense of taste, joint swelling or swelling in the hands or legs, and bone, muscle, or joint pain.
- Call your doctor if you develop severe bone, muscle, or joint pain.

Tell your doctor about any side effect that bothers you or that does not go away.

These are not all the side effects with FOSAMAX. Ask your doctor or pharmacist for more information.

How do I store FOSAMAX?

- Store FOSAMAX at room temperature, 59 to 86°F (15 to 30°C).
- Safely discard FOSAMAX that is out-of-date or no longer needed.
- Keep FOSAMAX and all medicines out of the reach of children.

General information about using FOSAMAX safely and effectively

Medicines are sometimes prescribed for conditions that are not mentioned in patient information leaflets. Do not use FOSAMAX for a condition for which it was not prescribed. Do not give FOSAMAX to other people, even if they have the same symptoms you have. It may harm them.

FOSAMAX is not indicated for use in children.

This leaflet is a summary of information about FOSAMAX. If you have any questions or concerns about FOSAMAX or osteoporosis, talk to your doctor, pharmacist, or other health care provider. You can ask your doctor or pharmacist for information about FOSAMAX written for health care providers. For more information, call 1-877-408-4699 (toll-free) or visit the following website: www.fosamax.com.

What are the ingredients in FOSAMAX?

FOSAMAX contains alendronate sodium as the active ingredient and the following inactive ingredients: cellulose, lactose, croscarmellose sodium and magnesium stearate. The 10 mg tablet also contains carnauba wax.

What should I know about osteoporosis?

Normally your bones are being rebuilt all the time. First, old bone is removed (resorbed). Then a similar amount of new bone is formed. This balanced process keeps your skeleton healthy and strong.

Osteoporosis is a thinning and weakening of the bones. It is common in women after menopause, and may also occur in men. In osteoporosis, bone is removed faster than it is formed, so overall bone mass is lost and bones become weaker. Therefore, keeping bone mass is important to keep your bones healthy. In both men and women, osteoporosis may also be caused by certain medicines called corticosteroids.

At first, osteoporosis usually has no symptoms, but it can cause fractures (broken bones). Fractures usually cause pain. Fractures of the bones of the spine may not be painful, but over time they can make you shorter. Eventually, your spine can curve and your body can become bent over. Fractures may happen during normal, everyday activity, such as lifting, or from minor injury that would normally not cause bones to break. Fractures most often occur at the hip, spine, or wrist. This can lead to pain, severe disability, or loss of ability to move around (mobility).

Who is at risk for osteoporosis?

Many things put people at risk of osteoporosis. The following people have a higher chance of getting osteoporosis:

Women who:

- Are going through or who are past menopause

Men who:

- Are elderly

People who:

- Are white (Caucasian) or oriental (Asian)
- Are thin
- Have family member with osteoporosis
- Do not get enough calcium or vitamin D
- Do not exercise
- Smoke
- Drink alcohol often
- Take bone thinning medicines (like prednisone or other corticosteroids) for a long time

What can I do to help prevent or treat osteoporosis?

In addition to FOSAMAX, your doctor may suggest one or more of the following lifestyle changes:

- Stop smoking. Smoking may increase your chance of getting osteoporosis.
- Reduce the use of alcohol. Too much alcohol may increase the risk of osteoporosis and injuries that can cause fractures.
- Exercise regularly. Like muscles, bones need exercise to stay strong and healthy. Exercise must be safe to prevent injuries, including fractures. Talk with your doctor before you begin any exercise program.
- Eat a balanced diet. Having enough calcium in your diet is important. Your doctor can advise you whether you need to change your diet or take any dietary supplements, such as calcium or vitamin D.

Rx Only

MERCK & CO., INC.
Whitehouse Station, NJ 08889, USA

Issued February 2008

9636808

PRINCIPAL DISPLAY PANEL

FOSAMAX, Tablets, 5 mg

FOSAMAX, Tablets, 10 mg

FOSAMAX, Tablets, 35 mg

FOSAMAX, Tablets, 70 mg